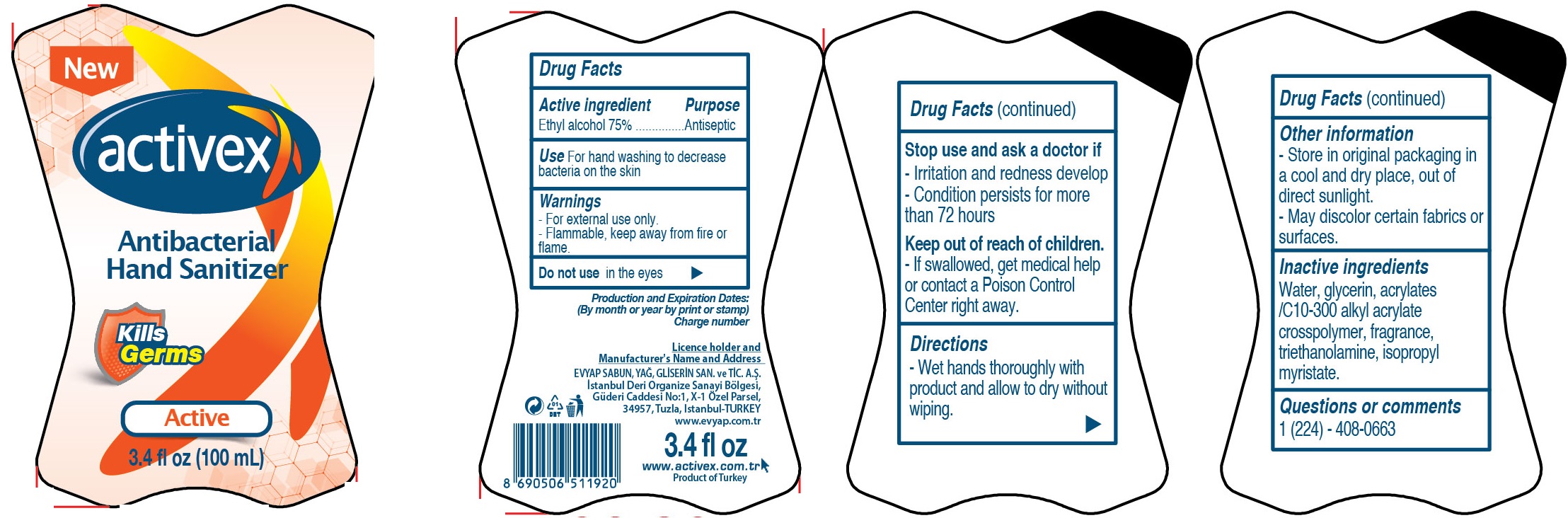 DRUG LABEL: Activex Antibacterial Hand Sanitizer Active
NDC: 64309-001 | Form: GEL
Manufacturer: Evyap Sabun Yag Gliserin Sanayi Ve Ticaret Anonim Sirketi
Category: otc | Type: HUMAN OTC DRUG LABEL
Date: 20201026

ACTIVE INGREDIENTS: ALCOHOL 0.75 mL/1 mL
INACTIVE INGREDIENTS: WATER; GLYCERIN; TROLAMINE; ISOPROPYL MYRISTATE

Activex Antibacterial Hand Sanitizer Active

Active ingredient

Ethyl alcohol 75%

Purpose

Antiseptic

Use

For hand washing to decrease bacteria on the skin

Warnings

- For external use only.
- Flammable, keep away from fire or flame.

Do not use

in the eyes

Stop use and ask a doctor if

-irritation and redness develop

-Condition persists for more than 72 hours

Keep out of reach of children.

-If swallowed, get medical help or contact a Poison Control Center right away.

Directions

-Wet hands thoroughly with product and allow to dry without wiping.

Other information

- Store in original packaging in a cool and dry place, out of direct sunlight.

- May discolor certain fabrics or surfaces.

Inactive ingredients

Water, glycerin, acrylates/C 10-300 alkyl acrylate crosspolymer, fragrance, triethanolamine, isopropyl myristate.

Questions or comments

1 (224) - 408-0663